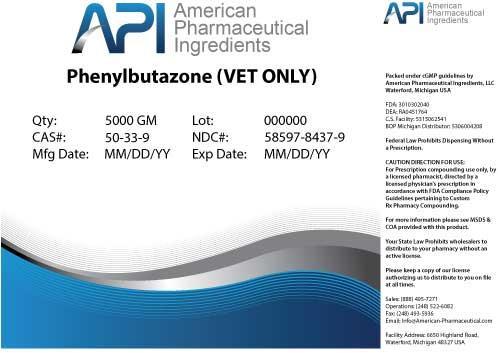 DRUG LABEL: Phenylbutazone
NDC: 58597-8437 | Form: POWDER
Manufacturer: AMERICAN PHARMACEUTICAL INGREDIENTS LLC
Category: other | Type: BULK INGREDIENT
Date: 20140428

ACTIVE INGREDIENTS: Phenylbutazone 1 g/1 g

Phenylbutazone